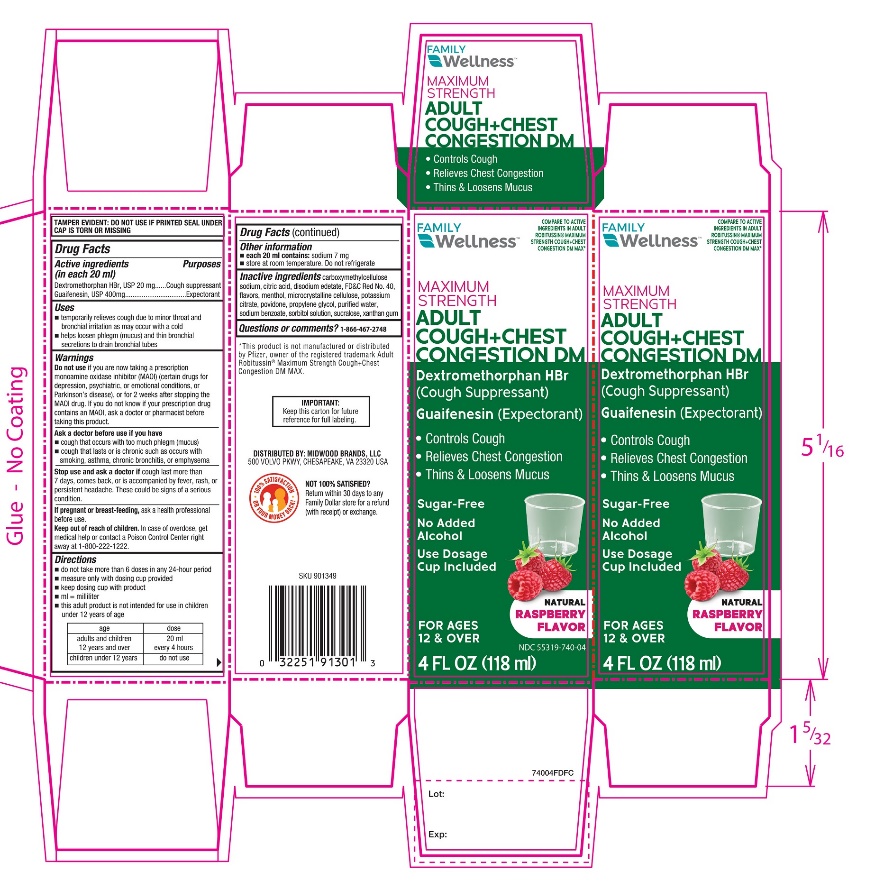 DRUG LABEL: Maximum Strength Adult Cough plus Chest Congestion DM
NDC: 55319-740 | Form: SOLUTION
Manufacturer: FAMILY DOLLAR SERVICES INC
Category: otc | Type: HUMAN OTC DRUG LABEL
Date: 20250925

ACTIVE INGREDIENTS: DEXTROMETHORPHAN HYDROBROMIDE 20 mg/20 mL; GUAIFENESIN 400 mg/20 mL
INACTIVE INGREDIENTS: ANHYDROUS CITRIC ACID; CARBOXYMETHYLCELLULOSE SODIUM, UNSPECIFIED; EDETATE DISODIUM; FD&C RED NO. 40; MENTHOL, UNSPECIFIED FORM; MICROCRYSTALLINE CELLULOSE; POVIDONE, UNSPECIFIED; PROPYLENE GLYCOL; WATER; POTASSIUM CITRATE; SODIUM BENZOATE; SORBITOL; SUCRALOSE; XANTHAN GUM

Maximum Strength Adult Cough+Chest Congestion DM Drug Facts

Active ingredients (in each 20 mL)

Dextromethorphan HBr, USP 20 mg

Guaifenesin, USP 400 mg

Purposes

Cough suppressant

Expectorant

Uses

- temporarily relieves cough due to minor throat and bronchial irritation as may occur with a cold
- helps loosen phlegm (mucus) and thin bronchial secretions to drain bronchial tubes

Do not use

if you are now taking a prescription monoamine oxidase inhibitor (MAOI) (certain drugs for depression, psychiatric, or emotional conditions, or Parkinson’s disease), or for 2 weeks after stopping the MAOI drug. If you do not know if your prescription drug contains an MAOI, ask a doctor or pharmacist before taking this product.

Ask a doctor before use if you have

- cough that occurs with too much phlegm (mucus)
- cough that lasts or is chronic such as occurs with smoking, asthma, chronic bronchitis, or emphysema

Stop use and ask a doctor if

cough lasts for more than 7 days, comes back, or is accompanied by fever, rash, or persistent headache. A persistent cough may be a sign of a serious condition.

If pregnant or breast-feeding,

ask a health professional before use.

Keep out of reach of children.

In case of overdose, get medical help or contact a Poison Control Center right away (1-800-222-1222).

Directions

- do not take more than 6 doses in any 24-hour period
- measure only with dosing cup provided
- keep dosing cup with product
- mL = milliliter
- this adult product is not intended for use in children under 12 years of age

age | dose
adults and children 12 years and over | 20 mL every 4 hours
children under 12 years | do not use

Other information

- each 20 mL contains:sodium 7 mg
- store at room temperature. Do not refrigerate.

Inactive ingredients

anhydrous citric acid, carboxymethylcellulose sodium, edetate disodium, FD&C Red No. 40, flavor, menthol, microcrystalline cellulose, povidone, propylene glycol, purified water, potassium citrate, sodium benzoate, sorbitol solution, sucralose, xanthan gum.

Questions or comments?

1-866-467-2748

Package/Label Principal Display Panel

Compare to the active ingredients of Robitussin® Maximum Strength Cough + Chest Congestion DM MAX*

NDC# 55319-740-04

Maximum Strength

Adult

Cough+Chest

Congestion DM

Dextromethorphan HBr (Cough Suppressant)

Guaifenesin (Expectorant)

- Controls cough
- Relieves Chest Congestion
- Thins and Loosens Mucus

Sugar-Free

No Added Alcohol

Use Dosage Cup Included

Natural Raspberry Flavor

For Ages 12 & Over

4 FL OZ (118 mL)

Distributed By:

*This product is not manufactured or distributed by Pfizer, owner of the registered trademark Adult Robitussin®Maximum Strength Cough + Congestion DM MAX.